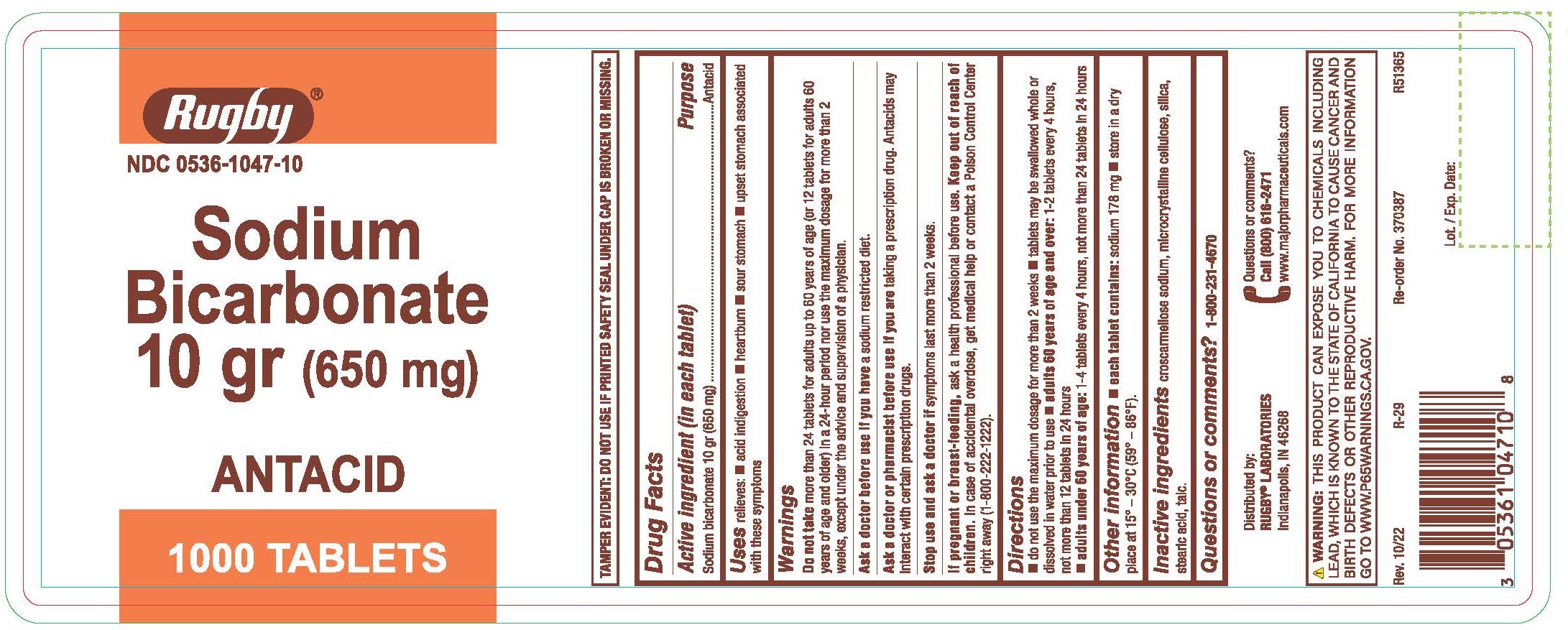 DRUG LABEL: Sodium Bicarbonate Antacid
NDC: 0536-1047 | Form: TABLET
Manufacturer: Rugby Laboratories
Category: otc | Type: HUMAN OTC DRUG LABEL
Date: 20240111

ACTIVE INGREDIENTS: SODIUM BICARBONATE 650 mg/1 1
INACTIVE INGREDIENTS: CROSCARMELLOSE SODIUM; CELLULOSE, MICROCRYSTALLINE; STEARIC ACID; SILICON DIOXIDE; TALC

4624 - Rugby

Drug Facts

Active ingredient (in each tablet)

Sodium bicarbonate 10 gr (650 mg)

Purpose

Antacid

Uses

relieves:

- acid indigestion
- heartburn
- sour stomach
- upset stomach associated with these symptoms

Warnings

Do not take more than 24 tablets for adults up to 60 years of age (or 12 tablets for adults 60 yeasr of age and older) in a 24-hour period nor use the maximum dosage for more than 2 weeks, except under the advice and supervision of a physician.

Ask a doctor before use if you have a sodium restricted diet.

Ask a doctor or pharmacist before use if you are taking a prescription drug.

Antacids may interact with certain prescription drugs.

Stop use and ask a doctor if symptoms last more than 2 weeks

PREGNANCY OR BREAST FEEDING

If pregnant or breast-feeding, ask a health professional before use.

Keep out of reach of children.

OVERDOSAGE

In case of accidental overdose, get medical help or contact a Poison Control Center right away (1-800-222-1222).

Directions

- do not use the maximum dosage for more than 2 weeks
- tablets may be swallowed whole or dissolved in water prior to use
- adults 60 years of age and over: 1-2 tablets every 4 hours, not more than 12 tablets in 24 hours
- adults under 60 years of age: 1-4 tablets every 4 hours, not more than 24 tablets in 24 hours

Other information

- each tablet contains: sodium 178 mg
- store in a dry place at 15° – 30°C (59° – 86°F).

Inactive ingredients

croscarmellose sodium, microcrystalline cellulose, silica, stearic acid, talc.

Questions or comments?

1-800-231-4670

TAMPER EVIDENT: DO NOT USE IF PRINTED SAFETY SEAL UNDER CAP IS BROKEN OR MISSING.

Distributed by:

RUGBY® LABORATORIES

Indianapolis, IN 46268

Questions or comments?

Call (800) 616-2471

www.majorpharmaceuticals.com

WARNING: THIS PRODUCT CAN EXPOSE YOU TO CHEMICALS INCLUDING

LEAD, WHICH IS KNOWN TO THE STATE OF CALIFORNIA TO CAUSE CANCER AND

BIRTH DEFECTS OR OTHER REPRODUCTIVE HARM. FOR MORE INFORMATION

GO TO WWW.P65WARNINGS.CA.GOV.

Rev. 10/22 R-29

PACKAGE LABEL

Rugby

NDC 0536-1047-10

Sodium Bicarbonate 10 gr (650 mg)

ANTACID

1000 TABLETS